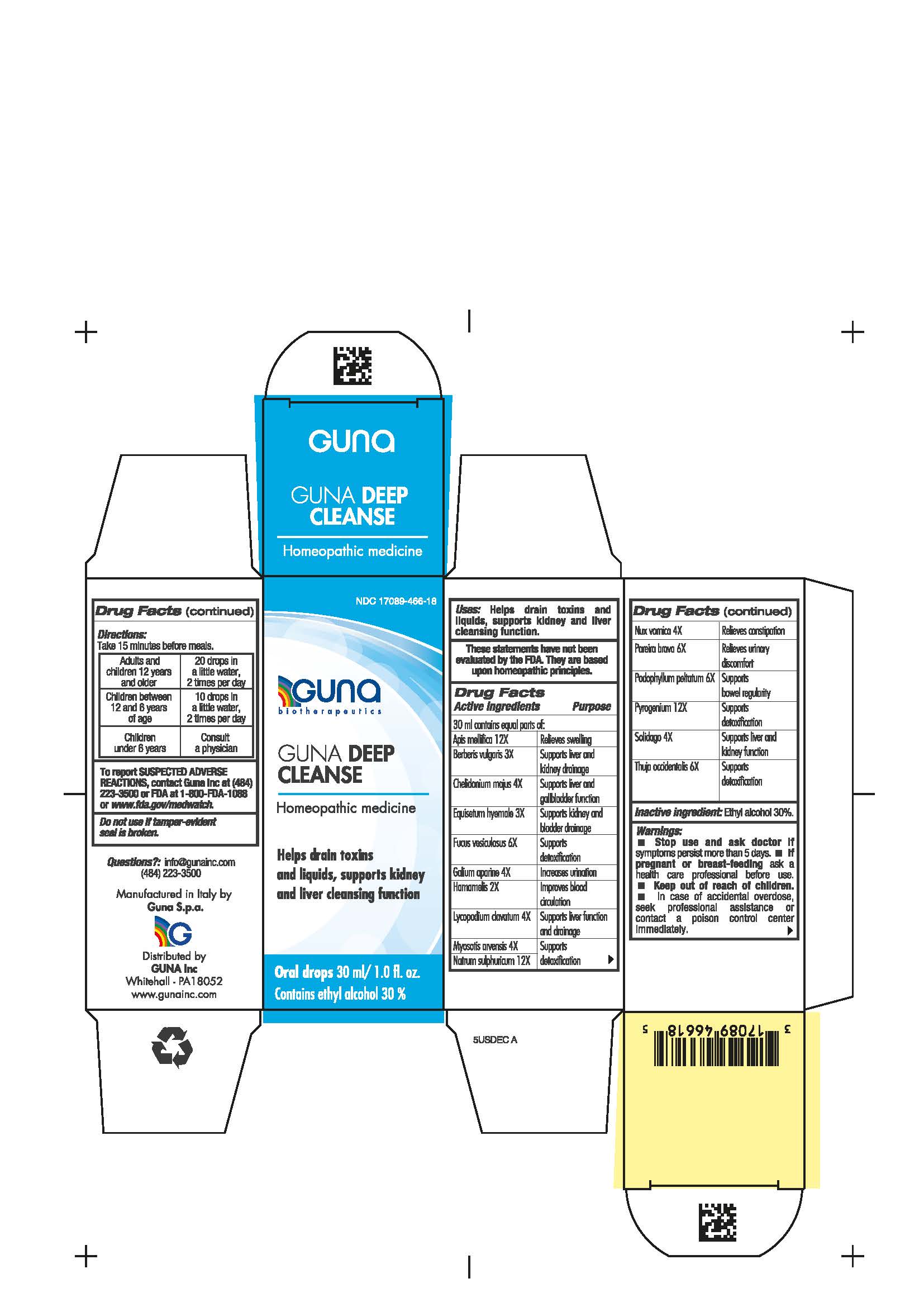 DRUG LABEL: GUNA DEEP CLEANSE
NDC: 17089-466 | Form: SOLUTION/ DROPS
Manufacturer: Guna spa
Category: homeopathic | Type: HUMAN OTC DRUG LABEL
Date: 20200924

ACTIVE INGREDIENTS: CHELIDONIUM MAJUS ROOT 4 [hp_X]/30 mL; LYCOPODIUM CLAVATUM SPORE 4 [hp_X]/30 mL; SODIUM SULFATE 12 [hp_X]/30 mL; SOLIDAGO VIRGAUREA FLOWERING TOP 4 [hp_X]/30 mL; RANCID BEEF 12 [hp_X]/30 mL; FUCUS VESICULOSUS 6 [hp_X]/30 mL; GALIUM APARINE WHOLE 4 [hp_X]/30 mL; THUJA OCCIDENTALIS LEAFY TWIG 6 [hp_X]/30 mL; MYOSOTIS ARVENSIS 4 [hp_X]/30 mL; STRYCHNOS NUX-VOMICA SEED 4 [hp_X]/30 mL; PODOPHYLLUM PELTATUM ROOT 6 [hp_X]/30 mL; CHONDRODENDRON TOMENTOSUM ROOT 6 [hp_X]/30 mL; APIS MELLIFERA 12 [hp_X]/30 mL; BERBERIS VULGARIS ROOT BARK 3 [hp_X]/30 mL; EQUISETUM HYEMALE WHOLE 3 [hp_X]/30 mL; HAMAMELIS VIRGINIANA ROOT BARK/STEM BARK 2 [hp_X]/30 mL
INACTIVE INGREDIENTS: ALCOHOL 9 mL/30 mL

GUNA DEEP CLEANSE

WHEN USING

Helps drain toxins and liquids,

supports kidney and liver cleansing function

Purpose

Helps drain toxins and liquids,

supports kidney and liver cleansing function

Active Ingredient(s)

Apis mellifica 12X Relieves swelling

Berberis vulgaris 3X Supports liver and kidney drainage

Chelidonoium majus 4X Supports liver and gallbladder function

Equisetum hyemale 3X Supports kidney and bladder drainage

Fucus vesiculosus 6X Supports detoxification

Galium aparine 4X Increases urination

Hamamelis 2X Improves blood circulation

Lycopodium clavatum 4X Supports liver function and drainage

Myosotis arvensis 4X Supports detoxification

Natrum sulphuricum 12X Supports detoxification

Nux vomica 4X Relieves constipation

Pareira brava 6X Relieves urinary discomfort

Podophyllum peltatum 6X Supports bowel regularity

Pyrogenium 12X Supports detoxification

Solidago 4X Supports liver and kidney function

Thuja occidentalis 6X Supports detoxification

INDICATIONS AND USAGE

Take 15 minutes before meals

Warnings

- Stop use and ask doctor if symptoms persist more than 5 days.
- If pregnant or breast-feeding ask a health professional before use.
- Keep out of reach of children.
- In case of accidental overdose, seek prfessional assistance or contact a Poison Control Center immediately
- Contains ethyl alcohol 30%

Do not use

if tamper-evident seal is broken

Stop use and ask doctor if symptoms persist more than 5 days.

Keep out of reach of children.

Directions

Take 15 minutes before meals.

Adults and children twelve years and older: 20 drops in a little water, 2 times per day

Children between 12 years and 6 years of age: 10 drops in a little water, 2 times per day

Children under 6 years: consult a physician

Other information

- No special storage conditions

Inactive ingredients

Inactive Ingredient: Ethyl alcohol 30%

ADVERSE REACTIONS

To Report SUSPECTED ADVERSE REACTIONS, contact Guna Inc at (484) 223-3500 or FDA at 1-800-FDA-1088 or www.fda.gov/medwatch